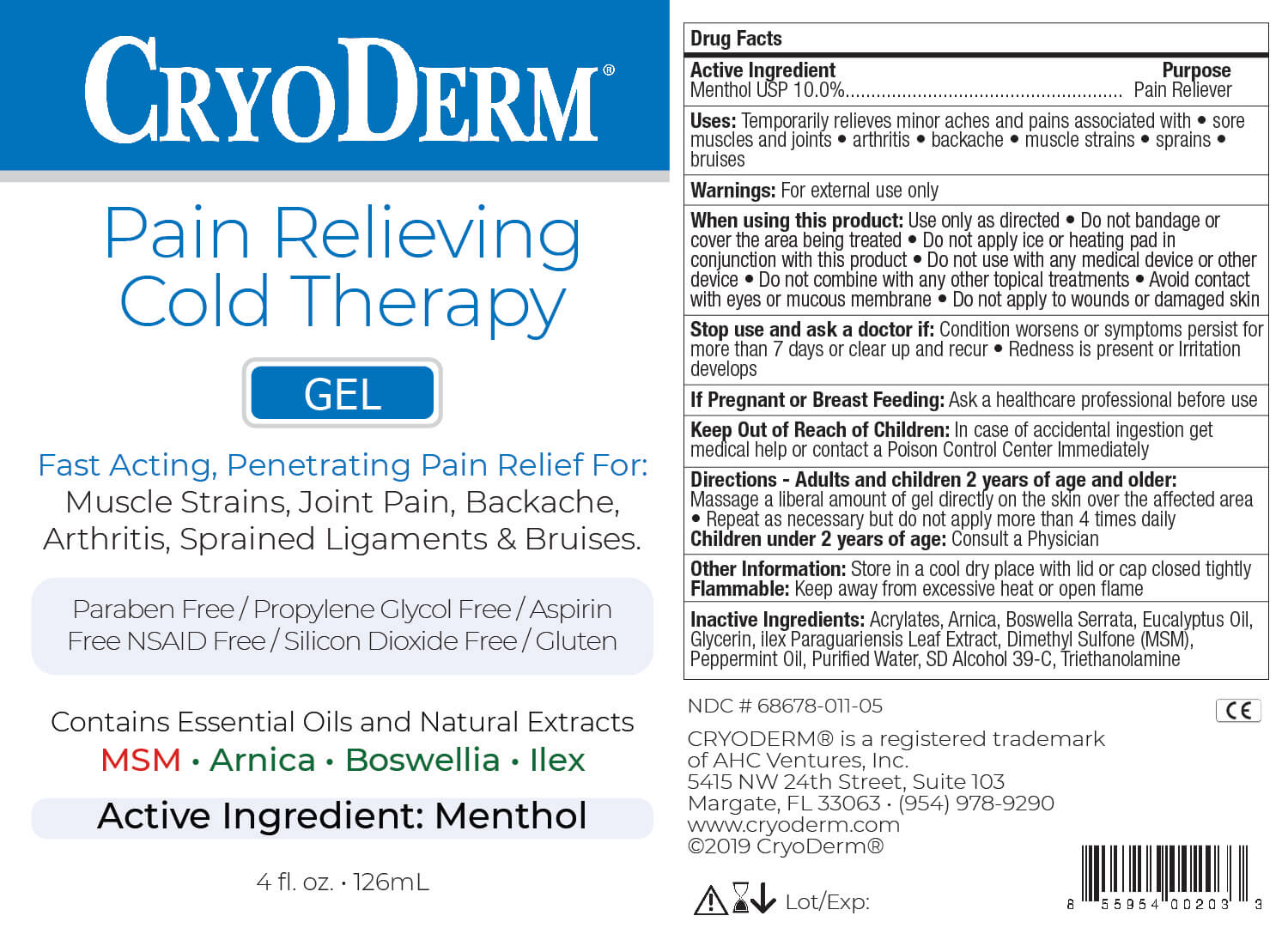 DRUG LABEL: Cold Therapy
NDC: 68678-011 | Form: GEL
Manufacturer: AHC VENTURES CORP DBA CRYODERM
Category: otc | Type: HUMAN OTC DRUG LABEL
Date: 20250902

ACTIVE INGREDIENTS: MENTHOL 10 g/100 mL
INACTIVE INGREDIENTS: ARNICA MONTANA 1 mL/100 mL; BOSWELLIA SERRATA WHOLE 1 mL/100 mL; EUCALYPTOL 0.05 mL/100 mL; GLYCERIN 5 mL/100 mL; ILEX PARAGUARIENSIS LEAF 1 mL/100 mL; DIMETHYL SULFONE 0.03 mL/100 mL; PEPPERMINT OIL 0.05 mL/100 mL; WATER 32.906 mL/100 mL; ALCOHOL 48.4 mL/100 mL; TROLAMINE 0.5 mL/100 mL; (C10-C30)ALKYL METHACRYLATE ESTER 0.004 mL/100 mL

Cold Therapy Menthol Gel

Active Ingredient

Menthol USP 10.0%

Purpose

Pain Reliever

Uses

Temporary relieves minor aches and pains associated with

- sore muscles and joints
- arthritis
- backache
- muscle strains
- sprains
- bruises

Warnings:

For external use only

When using this product:

Use only as directed. Do not bandage or use a heating pad or device. Avoid contact with eyes and mucous membranes. Do not apply to open wounds or damaged skin. Do not use with other ointment, creams, sprays or liniments. After applying wash hands thoroughly with cool water

Stop use and ask doctor if:

Condition worsens or symptoms persist for more than 7 days or clear up and recur. Redness is present or irritation develops

If Pregnant or Breast Feeding:

Ask a health professional before use

Keep Out of Reach of Children:

In case of accidental ingestion get medical help or contact a Poison Control Center immediately

Directions:

Adults and children 2 years and older:
Apply directly onto afected area without the need to rub, massage or bandage. Repeat as necessary but do not apply more than 4 times daily.
Children under 2 years of age: Consult a Physician

Other Information

Store in a cool dry place with lid or cap closed tightly

Flammable: Keep away from excessive heat or open flame

Inactive Ingredients:

Acrylates, Arnica, Boswellia Serrata, Eucalyptus Oil, Glycerin, Ilex Paraguariensis Leaf Extract, Dimethyl Sulfone, Peppermint Oil, Purified Water, SD Alcohol 39-C, Triethanolamine

PDP

CryoDerm

Pain Relieving Cold Therapy

Gel

Fast Acting, Penetrating Pain Relief For:

Muscle Strains, Joint Pain, Backache, Arthritis, Sprained Ligaments & Bruises.

Contains Essential Oils and Natural Extracts

MSM Arnica Boswellia Ilex

Active Ingredient: Menthol

4 fl. oz. 126mL